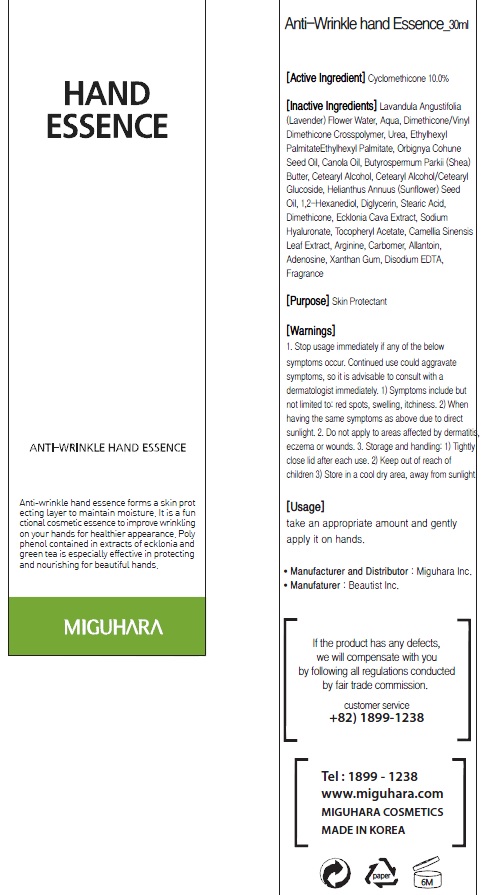 DRUG LABEL: Anti Wrinkle Hand Essence
NDC: 70380-120 | Form: CREAM
Manufacturer: MIGUHARA
Category: otc | Type: HUMAN OTC DRUG LABEL
Date: 20160219

ACTIVE INGREDIENTS: Glycerin 3 g/30 mL
INACTIVE INGREDIENTS: LAVANDULA ANGUSTIFOLIA FLOWER; Water

ACTIVE INGREDIENT

Active Ingredient: Glycerin 10.0%

INACTIVE INGREDIENT

Inactive Ingredients: Lavandula Angustifolia (Lavender) Flower Water, Aqua, Dimethicone/Vinyl Dimethicone Crosspolymer, Urea, Ethylhexyl PalmitateEthylhexyl Palmitate, Orbignya Cohune Seed Oil, Canola Oil, Butyrospermum Parkii (Shea) Butter, Cetearyl Alcohol, Cetearyl Alcohol/Cetearyl Glucoside, Helianthus Annuus (Sunflower) Seed Oil, 1,2-Hexanediol, Diglycerin, Stearic Acid, Dimethicone, Ecklonia Cava Extract, Sodium Hyaluronate, Tocopheryl Acetate, Camellia Sinensis Leaf Extract, Arginine, Carbomer, Allantoin, Adenosine, Xanthan Gum, Disodium EDTA, Fragrance

PURPOSE

Purpose: Skin Protectant

WARNINGS

1. Stop usage immediately if any of the below symptoms occur. Continued use could aggravate symptoms, so it is advisable to consult with a dermatologist immediately. 1) Symptoms include but not limited to: red spots, swelling, itchiness. 2) When having the same symptoms as above due to direct sunlight. 2. Do not apply to areas affected by dermatitis, eczema or wounds. 3. Storage and handling: 1) Tightly close lid after each use. 2 Keep out of reach of children 3) Store in a cool dry area, away from sunlight

KEEP OUT OF REACH OF CHILDREN

Usage

Usage: Take an appropriate amount and gently apply it on hands.

Usage

Usage: Take an appropriate amount and gently apply it on hands.